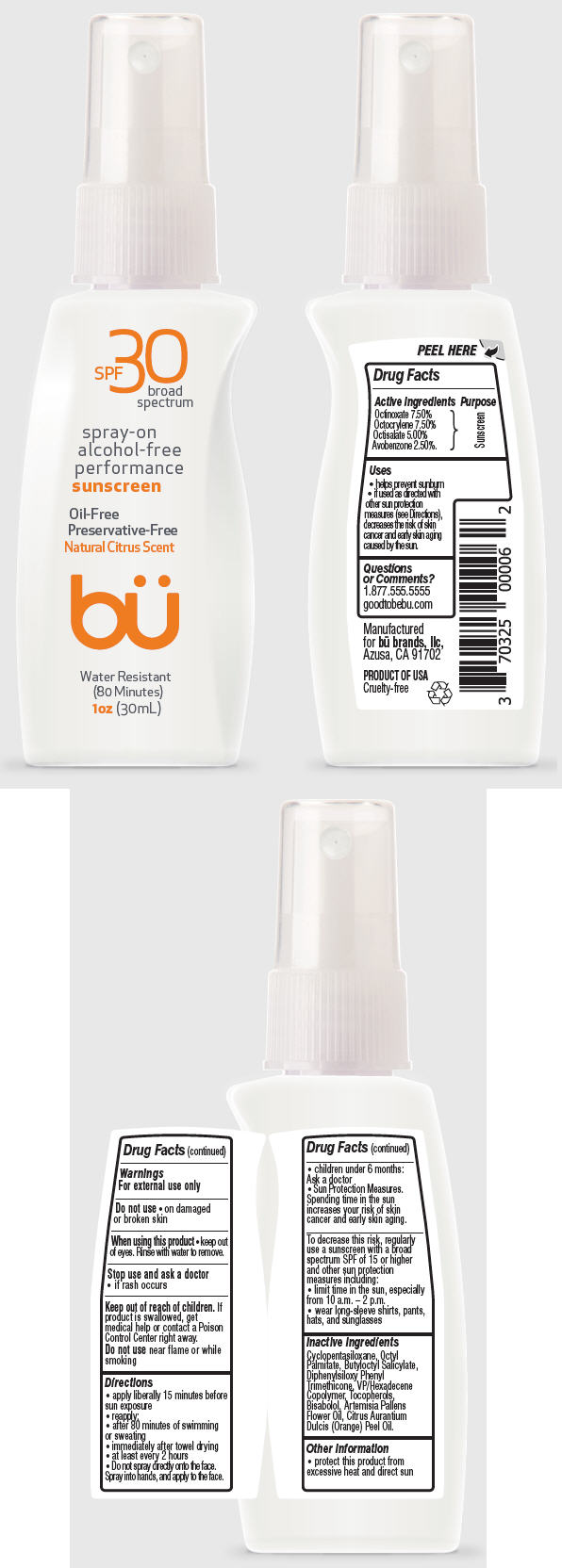 DRUG LABEL: bu SPF 30 Broad Spectrum Alcohol-Free Performance Sunscreen - Natural Citrus Scent
NDC: 70325-3003 | Form: SPRAY
Manufacturer: Bu Brands, LLC
Category: otc | Type: HUMAN OTC DRUG LABEL
Date: 20241017

ACTIVE INGREDIENTS: OCTINOXATE 7.5 g/100 mL; OCTOCRYLENE 7.5 g/100 mL; OCTISALATE 5 g/100 mL; AVOBENZONE 2.5 g/100 mL
INACTIVE INGREDIENTS: CYCLOMETHICONE 5; ETHYLHEXYL PALMITATE; BUTYLOCTYL SALICYLATE; DIPHENYLSILOXY PHENYL TRIMETHICONE; VINYLPYRROLIDONE/HEXADECENE COPOLYMER; TOCOPHEROL; .ALPHA.-BISABOLOL, (+/-)-; DAVANA OIL; ORANGE OIL

bü SPF 30 Broad Spectrum Spray on Alcohol-Free Performance Sunscreen - Natural Citrus Scent

Drug Facts

Active Ingredients

Octinoxate 7.50%
Octocrylene 7.50%
Octisalate 5.00%
Avobenzone 2.50%.

Purpose

Sunscreen

Uses

- helps prevent sunburn
- if used as directed with other sun protection measures (see Directions), decreases the risk of skin cancer and early skin aging caused by the sun.

Questions or Comments?

1.877.555.5555

goodtobebu.com

Warnings

For external use only

Do not use

- on damaged or broken skin

When using this product

- keep out of eyes. Rinse with water to remove.

Stop use and ask a doctor

- if rash occurs

Keep out of reach of children.If product is swallowed, get medical help or contact a Poison Control Center right away.

Do not usenear flame or while smoking

Directions

- apply liberally 15 minutes before sun exposure
- reapply:
  - after 80 minutes of swimming or sweating
  - immediately after towel drying
  - at least every 2 hours
- Do not spray directly onto the face. Spray into hands, and apply to the face.
- children under 6 months: Ask a doctor
- Sun Protection Measures. Spending time in the sun increases your risk of skin cancer and early skin aging.

To decrease this risk, regularly use a sunscreen with a broad spectrum SPF of 15 or higher and other sun protection measures including:

- limit time in the sun, especially from 10 a.m. – 2 p.m.
- wear long-sleeve shirts, pants, hats, and sunglasses

Inactive Ingredients

Cyclopentasiloxane, Octyl Palmitate, Butyloctyl Salicylate, Diphenylsiloxy Phenyl Trimethicone, VP/Hexadecene Copolymer, Tocopherols, Bisabolol, Artemisia Pallens Flower Oil, Citrus Aurantium Dulcis (Orange) Peel Oil.

Other Information

- protect this product from excessive heat and direct sun

PRINCIPAL DISPLAY PANEL - 30 mL Bottle Label

SPF30
broad
spectrum

spray-on
alcohol-free
performance
sunscreen

Oil-Free
Preservative-Free
Natural Citrus Scent

bü

Water Resistant
(80 Minutes)
1oz(30mL)